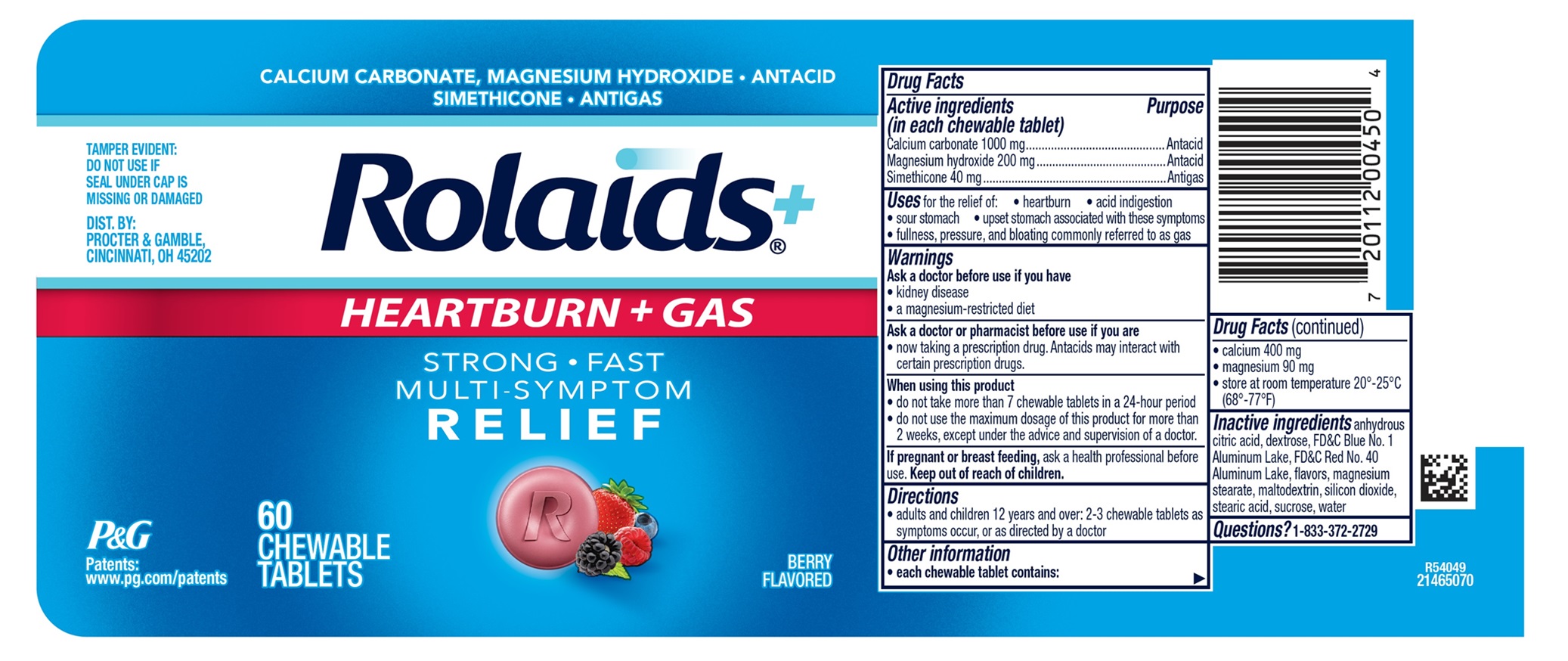 DRUG LABEL: Rolaids Heartburn plus Gas
NDC: 84126-343 | Form: TABLET, CHEWABLE
Manufacturer: The Procter & Gamble Manufacturing Company
Category: otc | Type: HUMAN OTC DRUG LABEL
Date: 20251201

ACTIVE INGREDIENTS: DIMETHICONE 40 mg/1 1; CALCIUM CARBONATE 1000 mg/1 1; MAGNESIUM HYDROXIDE 200 mg/1 1
INACTIVE INGREDIENTS: DEXTROSE; FD&C BLUE NO. 1 ALUMINUM LAKE; MAGNESIUM STEARATE; WATER; ANHYDROUS CITRIC ACID; MALTODEXTRIN; SILICON DIOXIDE; STEARIC ACID; SUCROSE; FD&C RED NO. 40 ALUMINUM LAKE

Rolaids HEARTBURN plus GAS

Drug Facts

Active ingredients (in each chewable tablet)

Calcium carbonate 1000 mg

Magnesium hydroxide 200 mg

Simethicone 40 mg

Purposes

Antacid

Antacid

Antigas

Uses

for the relief of:

- heartburn
- acid indigestion
- sour stomach
- upset stomach associated with these symptoms
- fullness, pressure, and bloating commonly referred to as gas

Warnings

Ask a doctor before use if you have

- kidney disease
- a magnesium-restricted diet

Ask a doctor or pharmacist before use if you are

- now taking a prescription drug. Antacids may interact with certain prescription drugs.

When using this product

- do not take more than 7 chewable tablets in a 24-hour period
- do not use the maximum dosage for more than 2 weeks, except under the advice and supervision of a doctor.

Directions

- adults and children 12 years and over; 2-3 chewable tablets as symptoms occur, or as directed by a doctor

Other information

- each chewable tablet contains:
- calcium 400 mg
- magnesium 90 mg
- store at room temperature 20°-25°C (68°-77°F).

Inactive ingredients

anhydrous citric acid, dextrose, FD&C Blue No. 1 Aluminum Lake, FD&C Red No. 40 Aluminum Lake, flavors, magnesium stearate, maltodextrin, silicon dioxide, stearic acid, sucrose, water

Questions?

1-833-372-2729

TAMPER EVIDENT: DO NOT USE IF SEAL UNDER CAP IS MISSING OR DAMAGED.

DIST. BY: PROCTER & GAMBLE,

CINCINNATI, OH 45202

PRINCIPAL DISPLAY PANEL

CALCIUM CARBONATE, MAGNESIUM HYDROXIDE • ANTACID SIMETHICONE • ANTIGAS

Rolaids

HEARTBURN + GAS

STRONG • FAST

MULTI-SYMPTOM

RELIEV

BERRY FLAVORED

60 CHEWABLE TABLETS